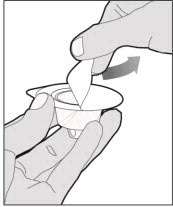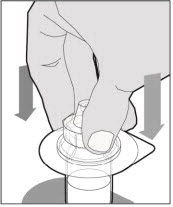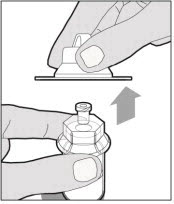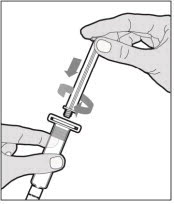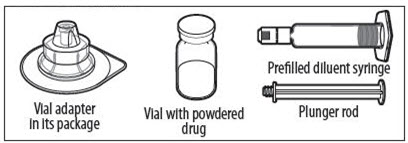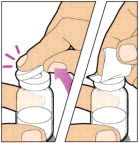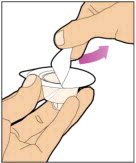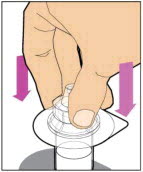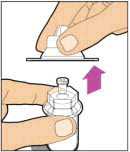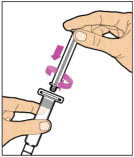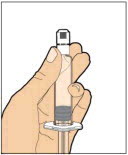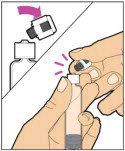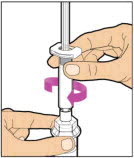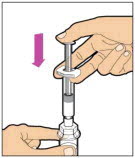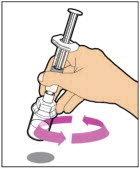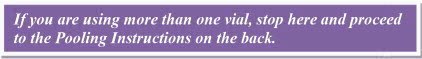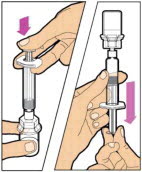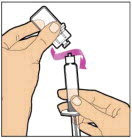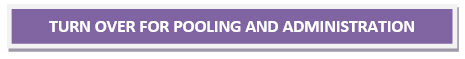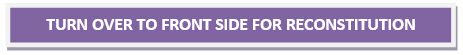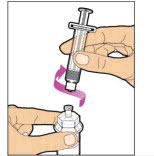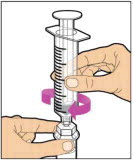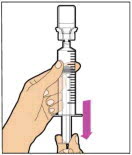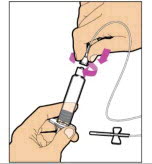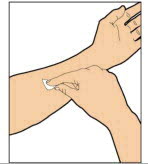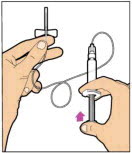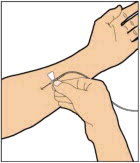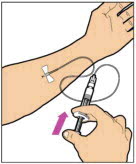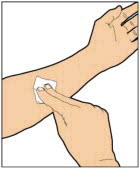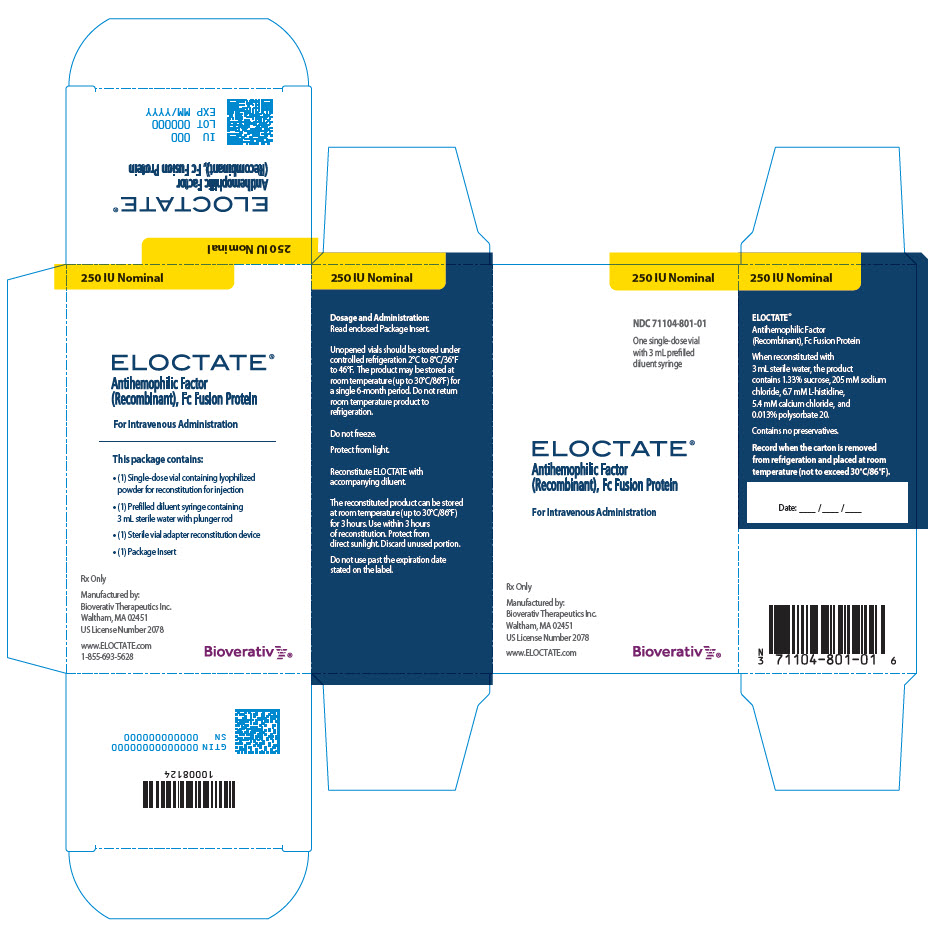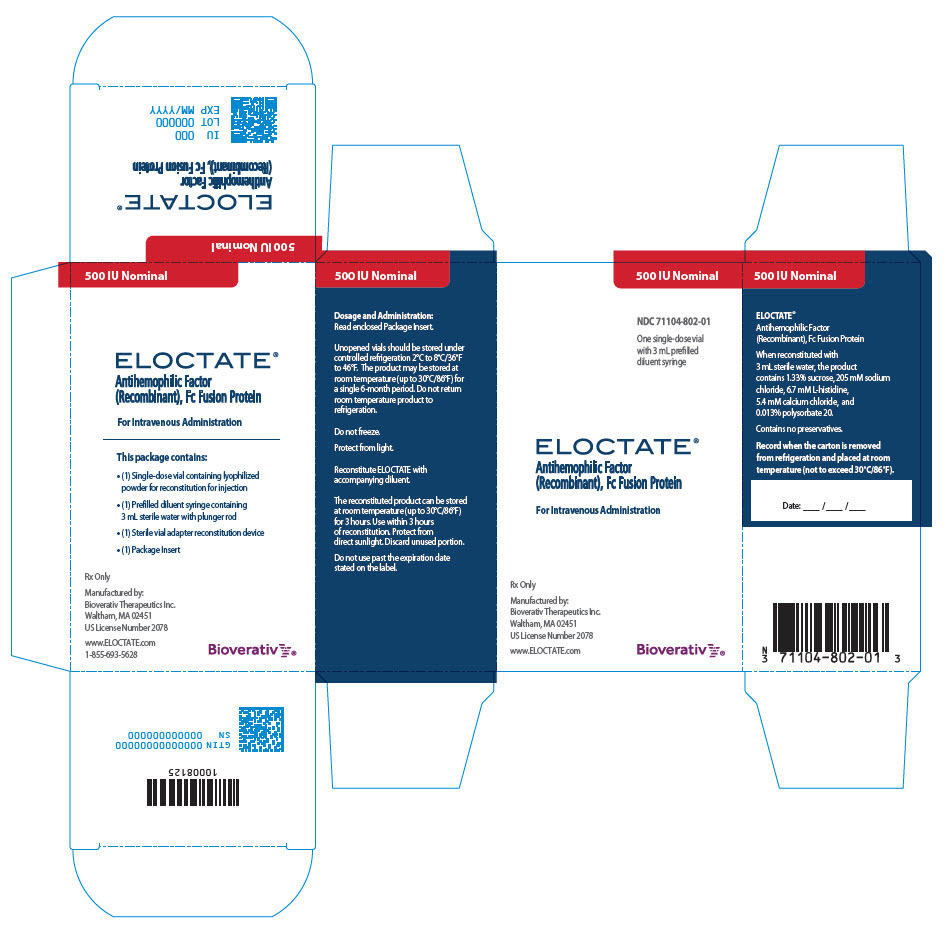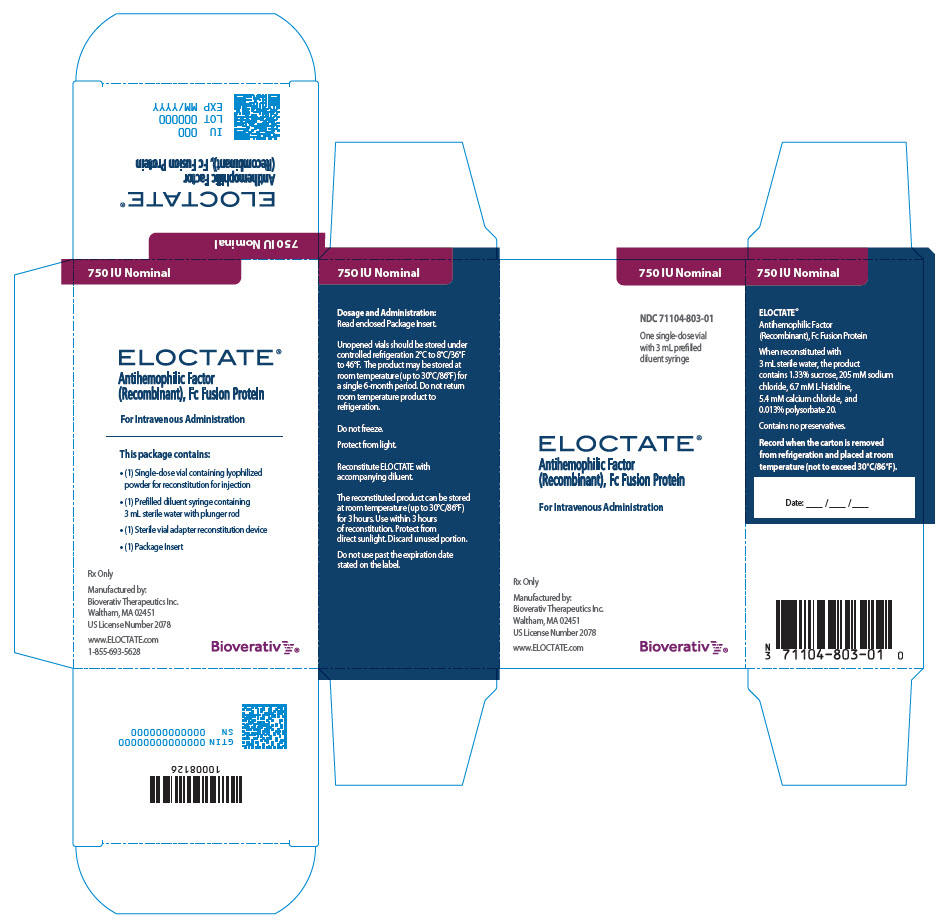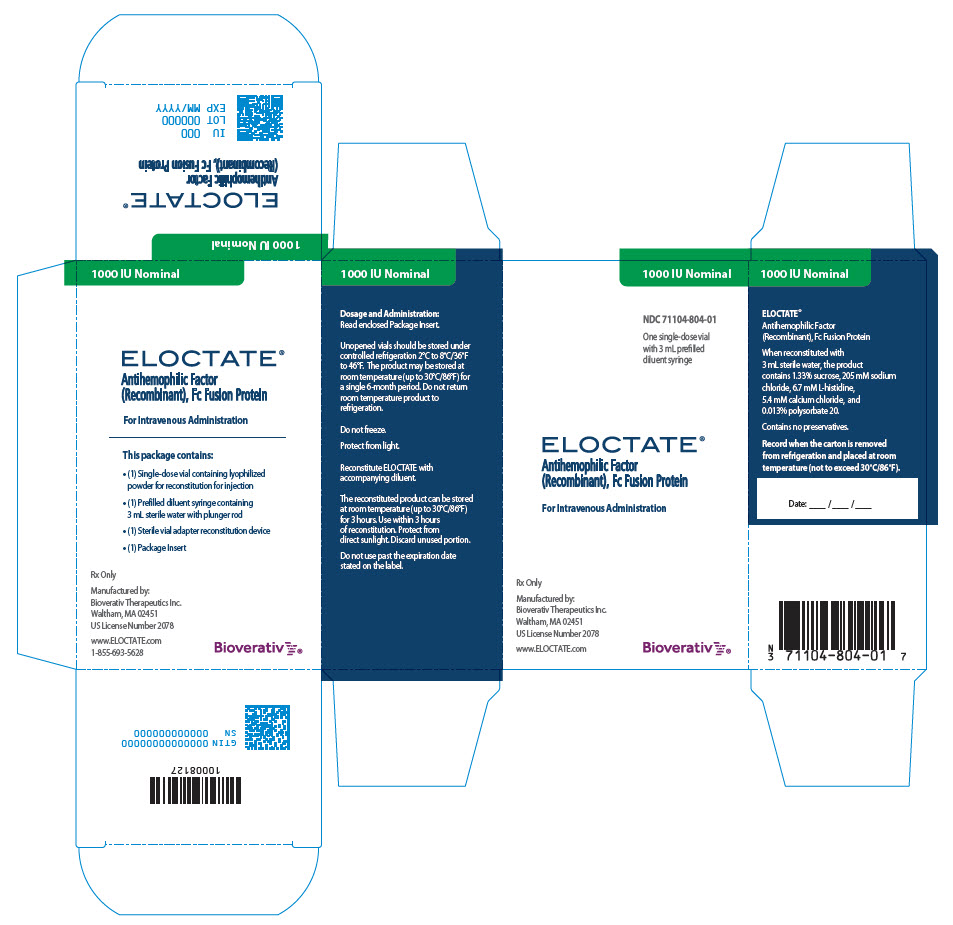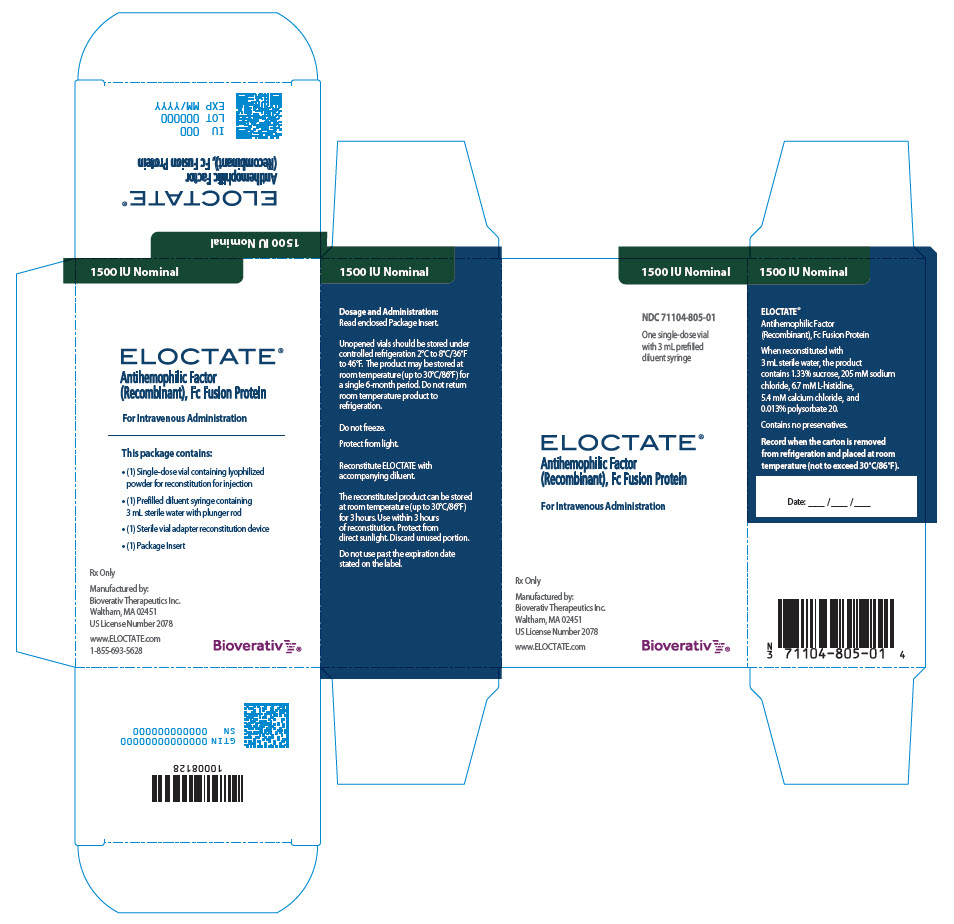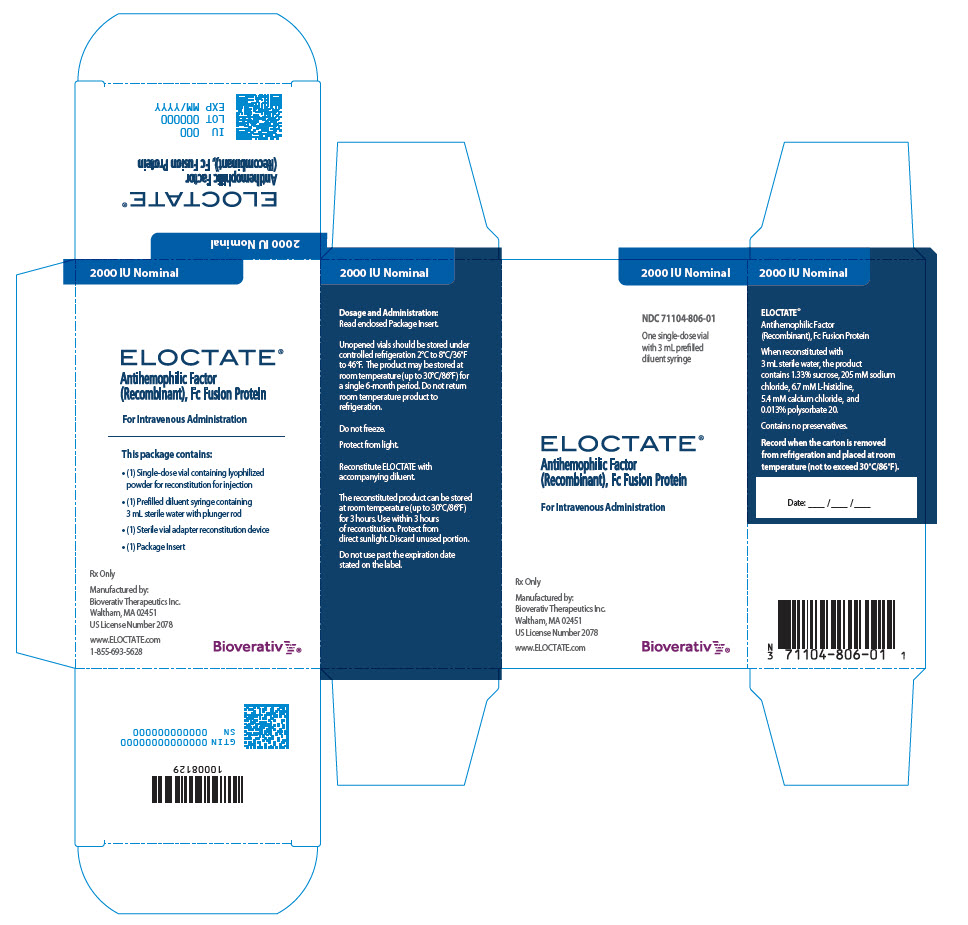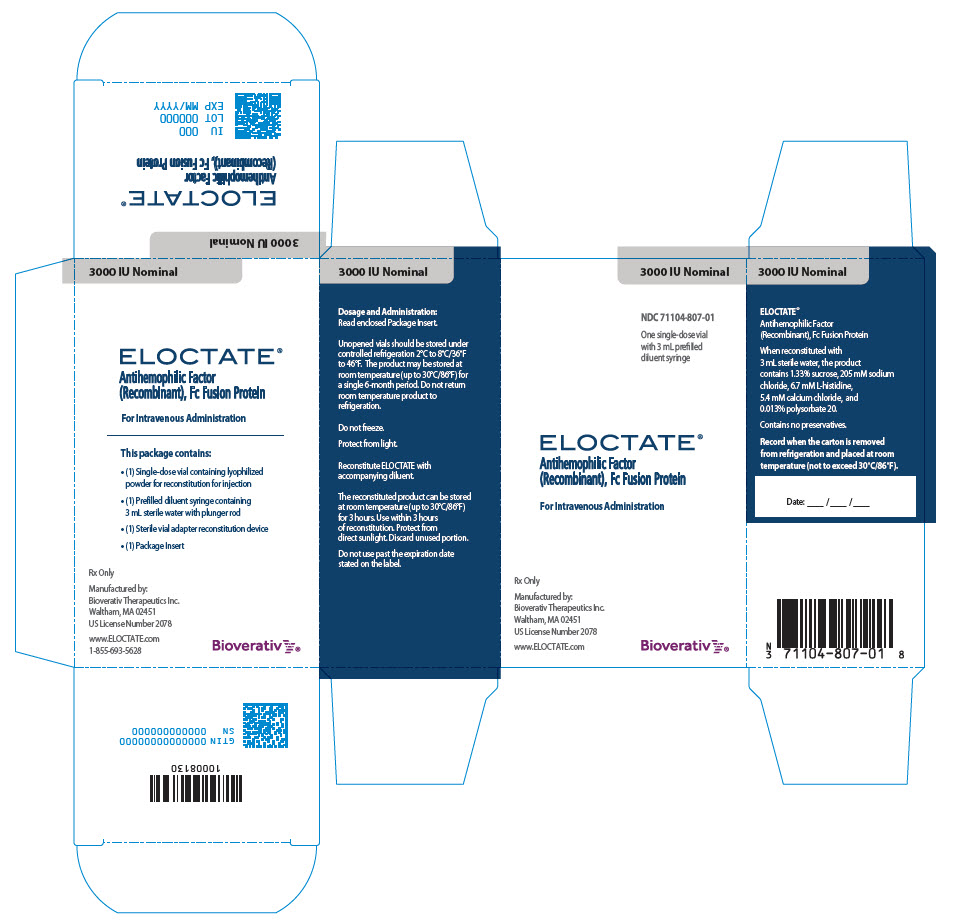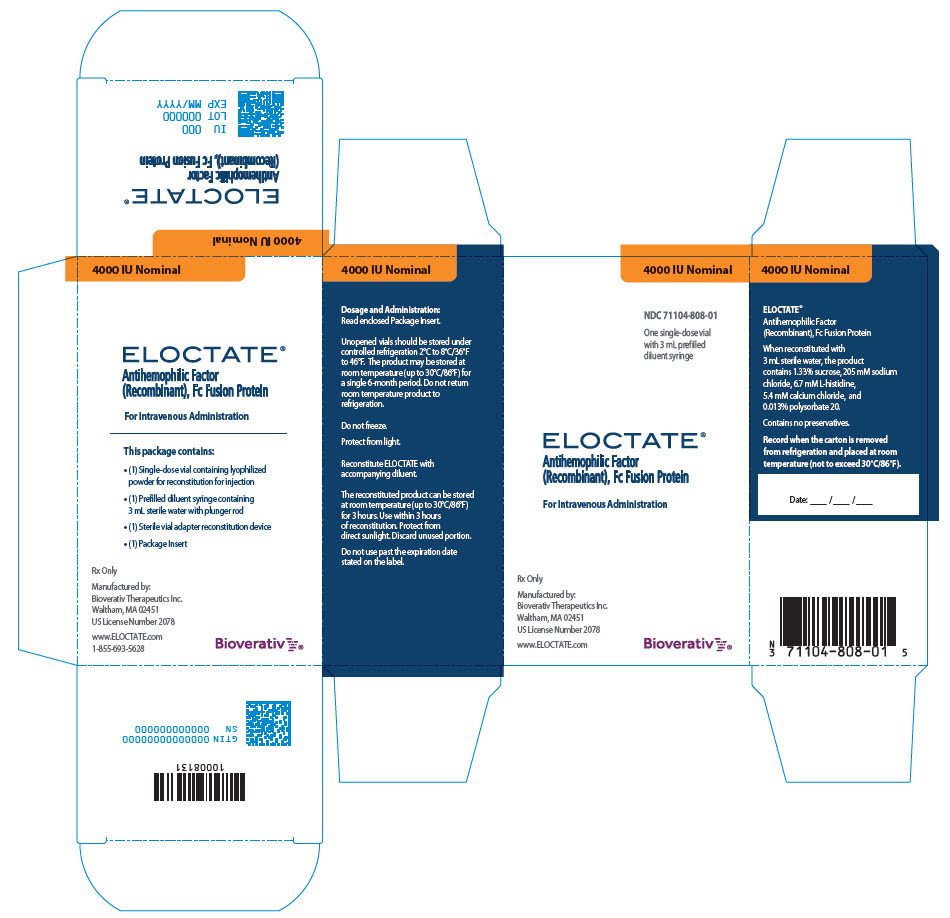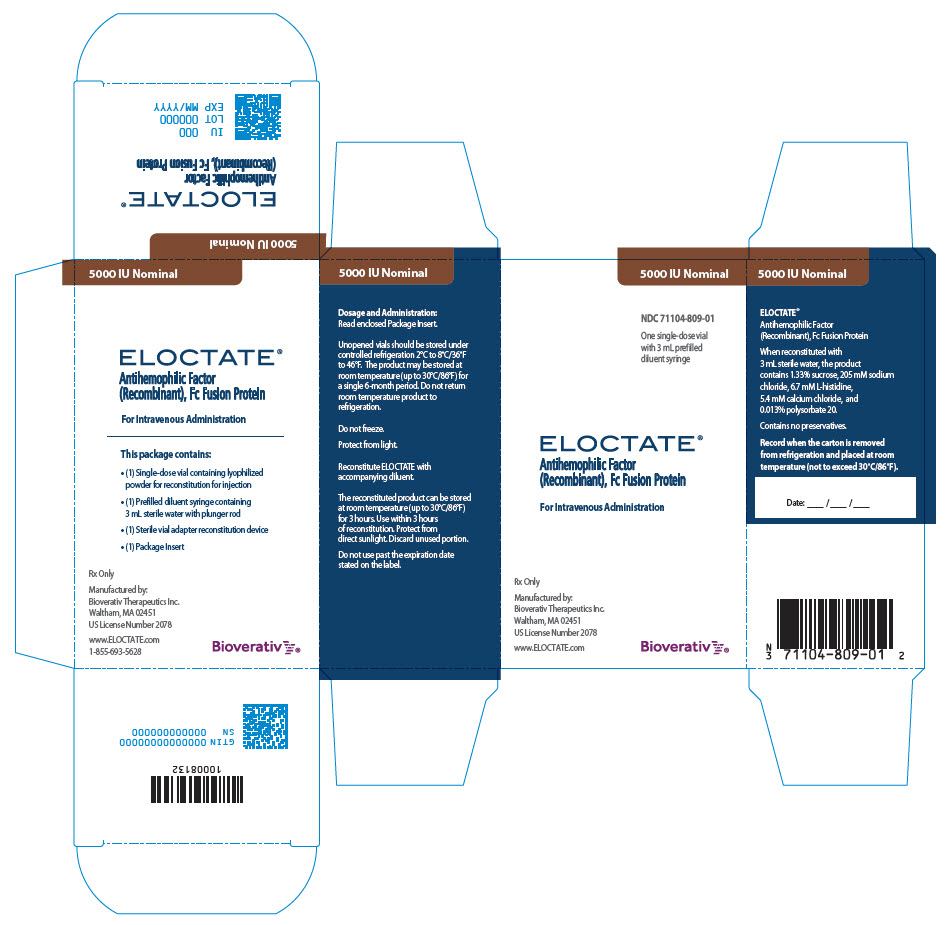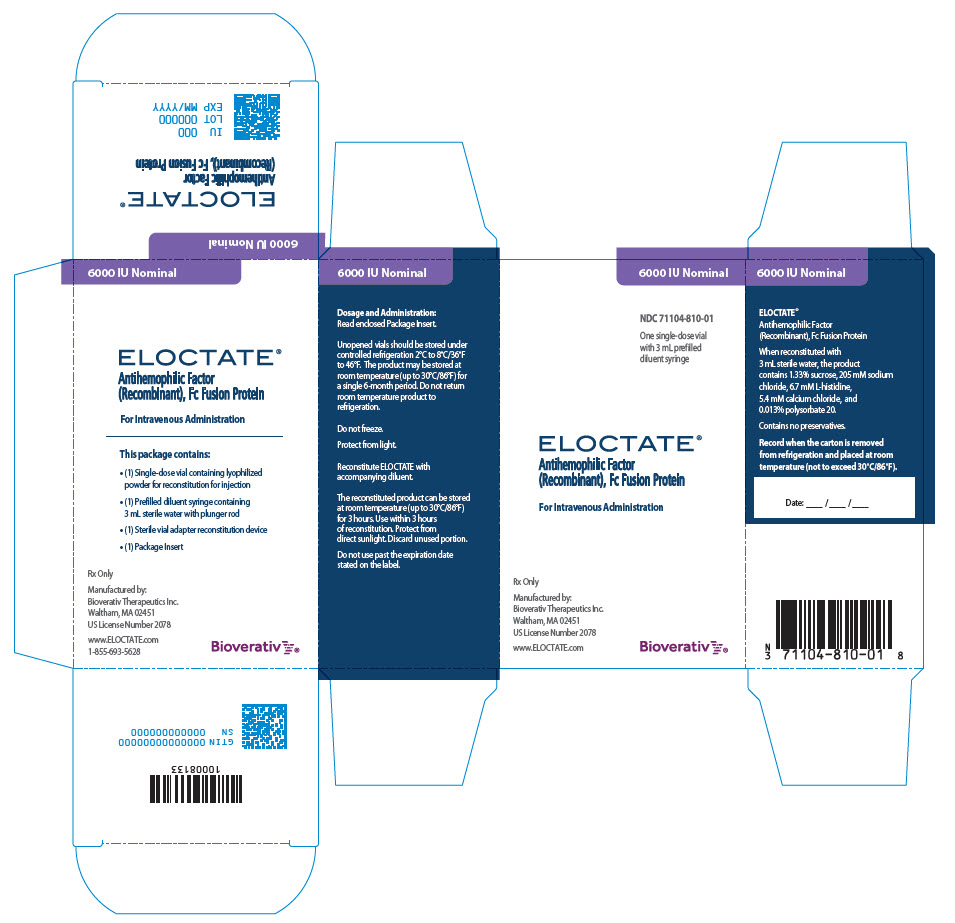 DRUG LABEL: ELOCTATE
NDC: 71104-801 | Form: KIT | Route: INTRAVENOUS
Manufacturer: Bioverativ Therapeutics Inc.
Category: other | Type: PLASMA DERIVATIVE
Date: 20230505

ACTIVE INGREDIENTS: EFMOROCTOCOG ALFA 250 [iU]/3 mL
INACTIVE INGREDIENTS: Histidine; sodium chloride; calcium chloride; sucrose; polysorbate 20; water

HIGHLIGHTS OF PRESCRIBING INFORMATION

These highlights do not include all the information needed to use ELOCTATE® safely and effectively. See full prescribing information for ELOCTATE.
ELOCTATE® [Antihemophilic factor (recombinant), Fc fusion protein], Lyophilized powder for solution for intravenous injection
Initial U.S. Approval: 2014

1 INDICATIONS AND USAGE

ELOCTATE, Antihemophilic Factor (Recombinant), Fc Fusion Protein, is a recombinant DNA derived, antihemophilic factor indicated in adults and children with Hemophilia A (congenital Factor VIII deficiency) for:

- On-demand treatment and control of bleeding episodes
- Perioperative management of bleeding
- Routine prophylaxis to reduce the frequency of bleeding episodes.

Limitation of Use

ELOCTATE is not indicated for the treatment of von Willebrand disease. (1)

2 DOSAGE AND ADMINISTRATION

For intravenous use after reconstitution only.

- Each vial of ELOCTATE is labeled with the amount of recombinant Factor VIII in international units (IU or unit). One unit per kilogram body weight will raise the Factor VIII level by 2% (IU/dL). (2.1)
- For on-demand treatment and control of bleeding episodes and perioperative management, calculate dose using the following formulas:
  Estimated Increment of Factor VIII (IU/dL or % of normal) = [Total Dose (IU)/body weight (kg)] x 2 (IU/dL per IU/kg)
  OR
  Required Dose (IU) = Body Weight (kg) x Desired Factor VIII Rise (IU/dL or % of normal) x 0.5 (IU/kg per IU/dL)
- For routine prophylaxis: 50 IU/kg every 4 days. Adjust dose based on patient response with dosing in the range of 25-65 IU/kg at 3-5 day intervals.
- For routine prophylaxis in children less than 6 years of age: 50 IU/kg twice weekly. Adjust dose based on patient response with dosing in the range of 25-65 IU/kg at 3-5 day intervals. More frequent or higher doses up to 80 IU/kg may be required. (2.1)

3 DOSAGE FORMS AND STRENGTHS

For injection: nominally 250, 500, 750, 1000, 1500, 2000, 3000, 4000, 5000, or 6000 IU, lyophilized powder in single-dose vials for reconstitution. (3)

4 CONTRAINDICATIONS

Do not use in patients who have had life-threatening hypersensitivity reactions, including anaphylaxis, to ELOCTATE or excipients of ELOCTATE (sucrose, sodium chloride, L-histidine, calcium chloride and polysorbate 20). (4)

5 WARNINGS AND PRECAUTIONS

- Hypersensitivity reactions, including anaphylaxis, are possible. Should symptoms occur, immediately discontinue ELOCTATE and initiate appropriate treatment. (5.1)
- Neutralizing antibodies (inhibitors) to Factor VIII have been reported. If expected plasma Factor VIII activity levels are not attained, or if bleeding is not controlled with an appropriate dose, perform an assay that measures Factor VIII inhibitor concentration. (5.2, 5.5)

6 ADVERSE REACTIONS

Previously Treated Patients (PTPs): The most frequently occurring adverse reactions (>0.5% of subjects) in clinical trials were arthralgia, malaise, myalgia, headache, and rash. (6)

Previously Untreated Patients (PUPs): The most frequently occurring adverse reactions (incidence ≥1%) from clinical trial were Factor VIII inhibition, device-related thrombosis, and rash papular. (6)

To report SUSPECTED ADVERSE REACTIONS, contact Bioverativ Therapeutics Inc. at 1-855-693-5628 or FDA at 1-800-FDA-1088 or www.fda.gov/medwatch.

8 USE IN SPECIFIC POPULATIONS

Pediatric: Clearance (based on per kg body weight) is higher (75%) in pediatric patients 1 to 5 years of age. Higher or more frequent dosing may be needed. (8.4)

FULL PRESCRIBING INFORMATION

1 INDICATIONS AND USAGE

ELOCTATE, Antihemophilic Factor (Recombinant), Fc Fusion Protein, is a recombinant DNA derived, antihemophilic factor indicated in adults and children with Hemophilia A (congenital Factor VIII deficiency) for:

- On-demand treatment and control of bleeding episodes,
- Perioperative management of bleeding,
- Routine prophylaxis to reduce the frequency of bleeding episodes.

Limitation of Use

ELOCTATE is not indicated for the treatment of von Willebrand disease.

2 DOSAGE AND ADMINISTRATION

For intravenous use after reconstitution only.

2.1 Dose

- Dose and duration of treatment depend on the severity of the Factor VIII deficiency, the location and extent of bleeding, and the patient's clinical condition. Careful monitoring of replacement therapy is necessary in cases of major surgery or life-threatening bleeding episodes.
- Each vial label of ELOCTATE states the Factor VIII potency in international units (IU). One IU corresponds to the activity of Factor VIII contained in one milliliter of normal human plasma.
- Potency assignment is determined using a chromogenic substrate assay. A field study^1 has indicated that plasma Factor VIII levels can be monitored using either a chromogenic substrate assay or a one stage clotting assay routinely used in US clinical laboratories.
- Calculation of the required dose of Factor VIII is based on the empirical finding that 1 IU of Factor VIII per kg body weight raises the plasma Factor VIII level by 2 IU/dL.

The expected in vivo peak increase in Factor VIII level expressed as IU/dL (or % of normal) is estimated using the following formula:

Estimated Increment of Factor VIII (IU/dL or % of normal) = [Total Dose (IU)/body weight (kg)] × 2 (IU/dL per IU/kg)

The dose to achieve a desired in vivo peak increase in Factor VIII level may be calculated using the following formula:

Dose (IU) = body weight (kg) × Desired Factor VIII Rise (IU/dL or % of normal) × 0.5 (IU/kg per IU/dL)

- Patients may vary in their pharmacokinetic (e.g., half-life, in vivo recovery) and clinical responses. Base the dose and frequency of ELOCTATE on the individual clinical response.
- Dose adjustment may be necessary in pediatric patients under six years of age [see Use in Specific Populations (8.4)]. For patients six years of age or older, dose adjustment is not usually required.

On-demand Treatment and Control of Bleeding Episodes

A guide for dosing ELOCTATE for the on-demand treatment and control of bleeding episodes is provided in Table 1. Consideration should be given to maintaining a Factor VIII activity at or above the target range.

Table 1: Dosing for Control of Bleeding Episodes
Type of Bleeding | Factor VIII Level Required (IU/dL or % of normal) | Dose (IU/kg) | Frequency of Dosing (hours) | Duration of Therapy (days)
Minor and Moderate Joint, superficial muscle/no neurovascular compromise (except iliopsoas), deep laceration and renal, superficial soft tissue, mucous membranes | 40-60 | 20-30 | Repeat every 24-48 hours (12 to 24 hours for patients less than 6 years of age) | Until the bleeding episode is resolved
Major Life or limb threatening hemorrhage, iliopsoas and deep muscle with neurovascular injury, retroperitoneum, intracranial, or gastrointestinal | 80-100 | 40-50 | Repeat every 12-24 hours (8 to 24 hours for patients less than 6 years of age) | Until bleeding is resolved (approximately 7-10 days)

Perioperative Management

A guide for dosing ELOCTATE during surgery (perioperative management) is provided in Table 2. Consideration should be given to maintaining a Factor VIII activity at or above the target range.

Table 2: Dosing for Perioperative Management
Type of Surgery | Factor VIII Level Required (IU/dL or % of normal) | Dose (IU/kg) | Frequency of Dosing (hours) | Duration of Therapy (days)
Minor Uncomplicated tooth extraction | 50-80 | 25-40 | Repeat every 24 hours (12-24 hours for patients less than 6 years of age) | At least 1 day until healing is achieved
Major Intracranial, intra-abdominal, or joint replacement surgery | 80-120 (pre and postoperative) | Preoperative: 40-60 Repeat: 40-50 | Preoperative dose of 40 to 60 IU/kg followed by a repeat dose of 40-50 IU/kg after 8-24 hours (6 to 24 for patients less than 6 years of age) and then every 24 hours to maintain FVIII activity within the target range | Until adequate wound healing, then continue therapy for at least 7 days to maintain a Factor VIII activity within the target range

Routine Prophylaxis

- The recommended starting regimen is 50 IU/kg of ELOCTATE administered every 4 days. Adjust the regimen based on patient response with dosing in the range of 25-65 IU/kg at 3-5 day intervals.
- For children <6 years of age, the recommended starting regimen is 50 IU/kg of ELOCTATE administered twice weekly. Adjust the regimen based on patient response with dosing in the range of 25-65 IU/kg at 3-5 day intervals. More frequent or higher doses up to 80 IU/kg may be required [see Use In Specific Populations (8.4), Clinical Pharmacology (12.3)].

2.2 Preparation and Reconstitution

1. Use aseptic technique (clean and germ free) and a flat work surface during the reconstitution procedure.
2. Allow the vial of ELOCTATE, containing the white to off-white lyophilized powder, and the pre-filled diluent syringe to reach room temperature before use.
3. Remove the plastic cap from the vial and wipe the rubber stopper of the vial with an alcohol wipe. Allow the rubber stopper to dry.
4. Completely remove the backing from the vial adapter package by peeling back the lid. Do not remove the vial adapter from the package or touch the inside of the package of the adapter.
5. Place the vial on a flat and solid surface and use one hand to hold the vial steady. Use the other hand to place the vial adapter over the vial. Place the adapter spike directly above the center of the rubber stopper and push the adapter straight down until the spike punctures the center of the vial stopper and is fully inserted.
6. Lift the package cover away from the vial adapter and discard the cover.
7. Hold the plunger rod at the circular disk. Place the tip of the plunger rod into the end of the syringe. Turn clockwise until it is securely attached. Only use the diluent syringe provided in the ELOCTATE package.
8. With one hand, hold the diluent syringe by the ridged part directly under the cap, with the cap pointing up. Do not use if the cap has been removed or is not securely attached.
9. With your other hand, grasp the cap and bend it at a 90° angle until it snaps off. After the cap snaps off, you will see the glass tip of the syringe. Do not touch the glass tip of the syringe or the inside of the cap.
10. With the vial sitting on a flat surface, insert the tip of the syringe into the adapter opening. Turn the syringe clockwise until it is securely attached to the adapter.
11. Slowly depress the plunger rod to inject all of the diluent into the vial. The plunger rod may rise slightly after this process. This is normal.
12. With the syringe still connected to the adapter, gently swirl the vial until the product is completely dissolved. Do not shake. The reconstituted solution should be clear to slightly opalescent and colorless. Do not use the reconstituted ELOCTATE if it contains visible particles or is cloudy.
13. Make sure the plunger rod is completely depressed. Turn the vial upside-down. Slowly pull on the plunger rod to draw the solution into the syringe. Be careful not to pull the plunger rod completely out of the syringe.
14. Gently unscrew the syringe from the vial adapter and dispose of the vial with the adapter still attached. Do not touch the syringe tip or the inside of the cap.
15. Use the reconstituted ELOCTATE as soon as possible, but no later than 3 hours after reconstitution. Do not touch the glass tip of the syringe if not used immediately after reconstitution. Protect from direct sunlight. Do not refrigerate after reconstitution.

To combine two or more vials of ELOCTATE, after step 12 above, follow these pooling steps:

1. Remove the diluent syringe from the vial adapter by turning it counterclockwise until it is completely detached.
2. Leave the vial adapter attached to the vial, as it is needed for attaching a large luer lock syringe (not included in kit). Do not detach the diluent syringe until ready to attach the large luer-lock syringe.
3. Attach a separate, large luer-lock syringe by turning clockwise until it is securely in place.
4. Slowly pull on the plunger rod to draw the solution into the syringe.
5. Repeat this pooling procedure with each vial that is needed to obtain the required dose. When pooling, do not detach the large luer-lock syringe until ready to attach it to the next vial (with vial adapter attached). Once you have pooled the required dose, proceed to administration using the large luer-lock syringe.

2.3 Administration

For intravenous injection only

- Inspect the reconstituted ELOCTATE solution visually for particulate matter and discoloration prior to administration. Do not use if particulate matter or discoloration is observed.
- Do not administer reconstituted ELOCTATE in the same tubing or container with other medications.

Administration Steps:

1. Attach the syringe to the connector end of the infusion set tubing by turning clockwise until it is securely in place.
2. Depress the plunger until all air is removed from the syringe and ELOCTATE has reached the end of the infusion set tubing. Do not push ELOCTATE solution through the needle.
3. Remove the protective needle cover from the infusion set tubing.
4. Perform intravenous bolus infusion. The rate of administration should be determined by the patient's comfort level, and no faster than 10 ml per minute. After infusing ELOCTATE, remove and properly discard the infusion set.

3 DOSAGE FORMS AND STRENGTHS

ELOCTATE is available as a white to off-white lyophilized powder in single-dose vials containing nominally 250, 500, 750, 1000, 1500, 2000, 3000, 4000, 5000 or 6000 international units (IU) per vial. The actual Factor VIII potency is labeled on each ELOCTATE vial.

4 CONTRAINDICATIONS

ELOCTATE is contraindicated in patients who have had life-threatening hypersensitivity reactions to ELOCTATE or its excipients (sucrose, sodium chloride, L-histidine, calcium chloride and polysorbate 20).

5 WARNINGS AND PRECAUTIONS

5.1 Hypersensitivity Reactions

Hypersensitivity reactions have been reported with ELOCTATE. Allergic-type hypersensitivity reactions, including anaphylaxis, have been reported with Factor VIII replacement products. Early signs of hypersensitivity reactions that can progress to anaphylaxis may include angioedema, chest tightness, dyspnea, wheezing, urticaria, and pruritus. Immediately discontinue administration and initiate appropriate treatment if hypersensitivity reactions occur.

5.2 Neutralizing Antibodies

Formation of neutralizing antibodies (inhibitors) to Factor VIII has been reported following administration of ELOCTATE. Monitor all patients for the development of Factor VIII inhibitors by appropriate clinical observations and laboratory tests. If the plasma Factor VIII level fails to increase as expected or if bleeding is not controlled after ELOCTATE administration, suspect the presence of an inhibitor (neutralizing antibody) [see Warnings and Precautions (5.5)].

5.3 Cardiovascular Risk Factors

Hemophilic patients with cardiovascular risk factors or diseases may be at the same risk to develop cardiovascular events as non-hemophilic patients when clotting has been normalized by treatment with Factor VIII.

5.4 Catheter-Related Complication

If a central venous access device (CVAD) is required, risk of CVAD-related complications including local infections, bacteremia, and catheter-site thrombosis should be considered [see Adverse Reactions (6)].

5.5 Monitoring Laboratory Tests

Monitor plasma Factor VIII activity by performing a validated test (e.g., one stage clotting assay), to confirm that adequate Factor VIII levels have been achieved and maintained [see Dosage and Administration (2)].

Monitor for the development of Factor VIII inhibitors. Perform a Bethesda inhibitor assay if expected Factor VIII plasma levels are not attained, or if bleeding is not controlled with the expected dose of ELOCTATE. Use Bethesda Units (BU) to report inhibitor levels.

6 ADVERSE REACTIONS

The most frequently occurring adverse reactions (incidence >0.5% of subjects) reported in previously treated patients (PTPs) clinical trials were arthralgia, malaise, myalgia, headache, and rash. The most frequently occurring adverse reactions (incidence ≥1.0% of subjects) reported in previously untreated patients (PUPs) clinical trials were Factor VIII inhibition, device-related thrombosis, and rash papular.

6.1 Clinical Trials Experience

Because clinical trials are conducted under widely varying conditions, adverse reaction rates observed in the clinical trials of one drug cannot be directly compared to rates in clinical trials of another drug and may not reflect the rates observed in practice.

Previously Treated Patients (PTPs)

ELOCTATE has been evaluated in 276 subjects in five completed studies in previously treated patients (PTPs) with severe Hemophilia A (<1% endogenous FVIII activity or a genetic mutation consistent with severe Hemophilia A) who received at least one dose of ELOCTATE as part of either routine prophylaxis, on-demand treatment of bleeding episodes or perioperative management. Sixty-nine (25.0%) were pediatric subjects <12 years of age, 25 (9.1%) were adolescents (12 to <18 years of age), and 182 (65.9%) were adults (18 years of age and older). There were 200 subjects treated for at least 104 weeks, 151 subjects treated for at least 156 weeks and 107 subjects treated for at least 208 weeks. The total number of exposure days (EDs) was 80,848 with a median of 294 (range 1-735) exposure days per subject. The subjects received a total of 82,024 injections with a median of 303.5 injections of ELOCTATE (range 1-755) per subject. Adverse events (AEs) were monitored for a total of 893.72 subject-years. Two subjects (0.7% of total 276) with cardiovascular risk factors each experienced a serious adverse reaction of myocardial infarction during the study.

Adverse reactions (ARs) were reported for 11 of 276 (4.0%) subjects treated with routine prophylaxis or episodic (on-demand) therapy. No age-specific differences in ARs were observed between pediatric and adult subjects. Table 3 summarizes the most frequently occurring adverse reactions in PTPs. Additional adverse reactions, each occurring in a single subject (incidence 0.4%), include dizziness, dysgeusia, bradycardia, hypertension, hot flush, angiopathy (investigator term: vascular pain after injection of study drug), cough, lower abdominal pain, back pain, joint swelling, chest pain, feeling cold, feeling hot, and procedural hypotension. Two subjects were withdrawn from study due to adverse reactions of rash and arthralgia. In the studies, no inhibitors were detected and no events of anaphylaxis were reported.

Table 3: Adverse Reactions Reported for ELOCTATE (N=276) in PTPs
MedDRA [MedDRA version 15.0] System Organ Class | Adverse Reactions | Number of Subjects n (%)
Nervous system disorders | Headache | 2 (0.7)
Skin and subcutaneous tissue disorders | Rash | 2 (0.7)
Musculoskeletal and connective tissue disorders | Arthralgia Myalgia | 2 (0.7) 2 (0.7)
General disorders and administration site conditions | Malaise | 2 (0.7)

Previously Untreated Patients (PUPs)

ELOCTATE safety was also evaluated in one completed study (PUPs study) in 103 subjects with severe hemophilia A (<1% endogenous FVIII activity). Overall, the median number of weeks on treatment was 64.24 weeks (range: 0.0–206.8 weeks). The number of subjects with at least 10 exposure days (EDs) was 87 (84.5%), at least 20 EDs was 85 (82.5%), and at least 50 EDs was 81 (78.6%).

Adverse drug reactions (ADRs) were reported in 29 of 103 (28.2%) subjects treated with ELOCTATE on routine prophylaxis, episodic, and/or immune tolerance induction (ITI) therapies. ADRs in PUPs are summarized in Table 4.

Table 4: Adverse Drug Reactions Reported for ELOCTATE in PUPs Study
MedDRA [MedDRA version 22.0] System Organ Class | Adverse Reactions | Number of Subjects (%) N=103 [The use of ELOCTATE for immune tolerance induction (ITI) was also investigated in 15 PUPs who had developed inhibitors (12 with high-titer inhibitors and 3 with low-titer inhibitors).]
Blood and lymphatic system disorders | Factor VIII inhibition [Two subjects who experienced events of factor VIII inhibition also experienced events of deep vein thrombosis in 1 subject and rash papular in another subject] | 28 (27.2)
General disorders and administration site conditions | Device related thrombosis [Includes device-related thrombosis and deep vein thrombosis, each event occurred in 1 subject with an indwelling central venous catheter.] | 2 (1.9)
Skin and subcutaneous tissues disorders | Rash papular | 1 (1.0)

Immunogenicity

Clinical trial subjects were monitored for neutralizing antibodies to Factor VIII. No PTPs developed confirmed neutralizing antibodies to Factor VIII. One 25 year old subject had a transient, positive, neutralizing antibody of 0.73 BU at week 14, which was not confirmed upon repeat testing 18 days later and thereafter.

In PUPs Study, development of neutralizing antibodies (inhibitors) was observed in 28 subjects, 14 of them had a high-titer inhibitor. Based on subjects with an inhibitor test following an exposure day (ED) milestone or who developed an inhibitor at any time during the study, the incidence of Factor VIII inhibitor development was:

- 28/90 subjects (31.1%) with at least 10 EDs
- 28/86 subjects (32.6%) with at least 50 EDs

The median time to inhibitor development for the 28 subjects was 9 EDs (interquartile range: 6.5–12).

The detection of antibodies that are reactive to Factor VIII is highly dependent on many factors, including the sensitivity and specificity of the assay, sample handling, timing of sample collection, concomitant medications and underlying disease. Therefore, it may be misleading to compare of the incidence of antibodies to ELOCTATE with the incidence of antibodies to other products.

6.2 Postmarketing Experience

The following adverse reactions have been identified during the postapproval use of ELOCTATE. Because these reactions are reported voluntarily from a population of uncertain size, it is not always possible to reliably estimate their frequency or establish a causal relationship to drug exposure.

Blood and lymphatic system disorders: Factor VIII inhibitor development

Immune system disorders: hypersensitivity

8 USE IN SPECIFIC POPULATIONS

8.1 Pregnancy

Risk Summary

There are no studies of ELOCTATE use in pregnant women to inform a drug-associated risk. The background risk of major birth defects and miscarriage in the indicated population is unknown; however, the background risk of major birth defects in the U.S. general population is 2-4% and of miscarriage is 15-20% of clinically recognized pregnancies.

Animal reproductive and developmental toxicity studies have not been conducted with ELOCTATE. In a placental transfer study, ELOCTATE was detected in murine fetal blood samples at approximately 1% of the maternal blood levels (range, 0.2% to 1.9%), 3 to 4 hours following dosing of pregnant mice with 260 to 650 times the clinical dose of 20 to 50 IU/kg ELOCTATE [see Data].

It is not known whether ELOCTATE can cause fetal harm when administered to a pregnant woman, or whether it can affect reproduction capacity. If ELOCTATE is clearly needed to treat a pregnant woman, advise the patient that the risks to the mother and to the fetus are unknown.

Data

Animal data

Pregnant, genetically-modified, FVIII-deficient mice (Hem A mice) were injected intravenously with a single dose of 400 IU (approximately 13,000 IU/kg) ELOCTATE at the end of pregnancy on Gestation Day 19. Blood samples were collected from the maternal mice and the fetuses 3 to 4 hours after dosing, and FVIII activity was measured in both maternal and fetal plasma using a FVIII chromogenic assay. After dosing pregnant HemA mice with ELOCTATE, FVIII activity in fetal blood was approximately 1% of the maternal blood levels, suggesting that placental transfer of ELOCTATE may occur. The relevance of these data to humans is unknown.

8.2 Lactation

Risk Summary

There is no information regarding the presence of ELOCTATE in human milk, its effects on the breastfed infant, or its effects on milk production. The developmental and health benefits of breastfeeding should be considered along with the mother's clinical need for ELOCTATE and any potential adverse effects on the breastfed infant from ELOCTATE or from the underlying maternal condition.

8.4 Pediatric Use

Safety and efficacy studies have been performed in 82 previously treated, pediatric patients (PTPs) <18 years of age who received at least one dose of ELOCTATE as part of routine prophylaxis, on-demand treatment of bleeding episodes, or perioperative management. Adolescent subjects were enrolled in the adult and adolescent safety and efficacy trial, and subjects <12 were enrolled in a pediatric trial. Safety and efficacy of ELOCTATE have been evaluated in 103 previously untreated pediatric patients (PUPs) <6 years of age (median 0.58 year; range: 0.02–4 years) in one study (PUPs Study) [see Adverse Reactions (6)].

Pharmacokinetic data from a pediatric study of the 54 evaluable subjects <12 years of age showed that no dose adjustment was required for patients ≥6 years old. Children age 1 to 5 years had a shorter half-life and higher clearance (adjusted for body weight); therefore, a higher dose or more frequent dosing may be needed in this age group [see Clinical Pharmacology (12.3)].

8.5 Geriatric Use

Clinical studies of ELOCTATE did not include sufficient numbers of subjects aged 65 and over to determine whether or not they respond differently from younger subjects.

11 DESCRIPTION

ELOCTATE, Antihemophilic Factor (Recombinant), Fc Fusion Protein, is a sterile, non-pyrogenic, white to off-white lyophilized powder for reconstitution for intravenous injection. The product is supplied in single-dose vials containing nominal potencies of 250, 500, 750, 1000, 1500, 2000 3000, 4000, 5000 or 6000 international units (IU). Each vial of ELOCTATE is labeled with the actual content in IU. The powder for injection is reconstituted with 3 mL sterile water for injection (SWFI) supplied in a sterile prefilled syringe. The reconstituted solution should be essentially free of particles. The final product contains the excipients: sucrose, sodium chloride, L-histidine, calcium chloride and polysorbate 20. ELOCTATE contains no preservatives.

B-domain deleted recombinant Factor VIII, Fc fusion protein (BDD-rFVIIIFc) is the active ingredient in ELOCTATE. BDD-rFVIIIFc is a recombinant protein consisting of a B-domain deleted analogue of human Coagulation Factor VIII covalently linked to the human immunoglobulin G1 (IgG1) Fc domain sequence. The Factor VIII portion of the molecule has a 90 kDa heavy chain and an 80 kDa light chain (similar to endogenous Factor VIII), which are linked by 14 (of 908) amino acids from the central B-domain. The FVIII portion has post-translational modifications comparable to endogenous Factor VIII. The Fc domain of the molecule contains the hinge, CH2, and CH3 regions of IgG1. BDD-rFVIIIFc contains 1890 amino acids with an apparent molecular weight of 220 kDa. The majority of the expressed protein is proteolytically processed to a two chain molecule; however, ELOCTATE may also contain up to 39% of a single chain, non-processed form. Both molecules have been shown to have comparable Factor VIII activity.

BDD-rFVIIIFc is produced by recombinant DNA technology from a human embryonic kidney (HEK) cell line, which has been extensively characterized. The HEK cell line expresses BDD-rFVIIIFc into a defined, cell culture medium that does not contain any proteins derived from animal or human sources. BDD-rFVIIIFc is purified using a series of chromatography steps, including affinity capture with a recombinant, single chain antibody fragment produced in a yeast expression system. No human or animal derived proteins are used in the purification or formulation processes. The production process also incorporates two dedicated viral clearance steps - a detergent treatment step for inactivation and a 15 nm filtration step for removal of viruses.

12 CLINICAL PHARMACOLOGY

12.1 Mechanism of Action

ELOCTATE is a recombinant fusion protein that temporarily replaces the missing Coagulation Factor VIII needed for effective hemostasis. ELOCTATE contains the Fc region of human immunoglobulin G1 (IgG1), which binds to the neonatal Fc receptor (FcRn). FcRn is part of a naturally occurring pathway that delays lysosomal degradation of immunoglobulins by cycling them back into circulation and prolonging their plasma half-life.

12.2 Pharmacodynamics

Hemophilia A is a bleeding disorder characterized by a deficiency of functional coagulation Factor VIII, resulting in a prolonged, patient plasma clotting time as measured by the activated partial thromboplastin time (aPTT) assay. Treatment with ELOCTATE normalizes the aPTT over the effective dosing period.

12.3 Pharmacokinetics

The pharmacokinetics (PK) of ELOCTATE (rFVIIIFc) were evaluated in 28 subjects following a 10 minute intravenous infusion of a single dose of 50 IU/kg. The PK parameters were based on plasma FVIII activity measured by the one-stage clotting assay. The PK profile obtained at week 14, after repeated dosing, was comparable with the PK profile obtained after the first dose. The PK data demonstrate that ELOCTATE has a prolonged circulating half-life. Time to 1% was 5.10 days (95% CI: 4.54, 5.66). The terminal plasma half-life of ELOCTATE when compared against a currently marketed recombinant Factor VIII (ADVATE®) was 1.5 fold longer.

Pediatric and Adolescent Pharmacokinetics

Pharmacokinetic (PK) parameters of ELOCTATE were determined for adolescents (ages 12 to 17 years) in the adult and adolescent study and for children (ages 1 to 5 years and 6 to 11 years) in the pediatric study. Table 5 presents the PK parameters calculated from the pediatric data of 65 subjects, less than 18 years of age, after receiving a single 50 IU/kg dose.

Compared to adults and adolescents, body weight adjusted clearance was 75% higher in children 1 to 5 years of age. These results indicate a need for dose adjustments in children 1 to 5 years of age.

The PK evaluation of pediatric subjects, ages 6 to 17 years, showed that their PK profiles and arithmetic means of PK parameters are similar to those of adults. Therefore, for subjects 6 years and older, an age-based dose adjustment is not required.

Table 5: Comparison of PK Parameters of ELOCTATE by Age
PK Parameters [PK parameters are presented in Arithmetic Mean (95% CI)] | Pediatric Study |  | Adult and Adolescent Study
 | 1 to 5 Years | 6 to 11 Years | 12 to 17 Years | Adults [The analysis included two adolescent subjects (15 and 16 years old)]
 | N=23 | N=31 | N=11 | N=28
Incremental Recovery (IU/dL per IU/kg) | 1.92 (1.80, 2.04) | 2.44 (2.07, 2.80) | 1.85 (1.58, 2.12) | 2.26 (2.13, 2.40)
AUC/Dose (IU x h/dL per IU/kg) | 30.0 (26.5, 33.6) | 41.9 (34.0, 49.8) | 38.7 (34.3, 43.1) | 54.1 (47.0, 61.1)
t½ (h) | 12.7 (11.2, 14.1) | 14.9 (12.0, 17.8) | 16.4 (14.1, 18.6) | 19.7 (17.4, 22.0)
MRT (h) | 17.2 (15.4, 19.1) | 20.9 (17.1, 24.7) | 23.1 (19.9, 26.4) | 26.1 (23.2, 28.9)
CL (mL/h/kg) | 3.60 (3.13, 4.07) | 2.78 (2.44, 3.13) | 2.66 (2.34, 2.98) | 2.06 (1.78, 2.34)
Vss (mL/kg) | 58.6 (54.9, 62.3) | 52.1 (45.3, 59.0) | 60.3 (53.3, 67.3) | 49.5 (46.9, 52.2)
Abbreviations: CI = confidence interval; AUC = area under the FVIII activity time curve; t1/2 = terminal half-life; MRT = mean residence time; CL = body weight adjusted clearance; Vss = body weight adjusted volume of distribution at steady state

13 NONCLINICAL TOXICOLOGY

13.1 Carcinogenesis, Mutagenesis, Impairment of Fertility

Long-term animal studies investigating the carcinogenic effects of ELOCTATE have not been conducted. In vitro and in vivo testing of ELOCTATE for mutagenicity or effects on fertility was not performed.

14 CLINICAL STUDIES

The safety and efficacy of ELOCTATE was evaluated in two multicenter, prospective, open-label clinical trials in previously treated patients (PTPs) (adult and adolescent study and pediatric study), and in an extension study.

The adult and adolescent study compared the efficacy of each of two prophylactic treatment regimens (individualized and fixed weekly) to episodic (on-demand) treatment; determined hemostatic efficacy in the treatment of bleeding episodes; and determined hemostatic efficacy during perioperative management in subjects undergoing major surgical procedures. The study enrolled a total of 165 previously treated male patients (PTPs) with severe Hemophilia A (<1% endogenous Factor VIII activity or a genetic mutation consistent with severe Hemophilia A). Subjects were aged 12 to 65 years, including 13 pediatric subjects aged 12 to 17 years. Of the 165 enrolled subjects, 164 received at least one dose of ELOCTATE and 163 (98%) were evaluable for efficacy. A total of 153 subjects (93%) completed the study.

The pediatric study evaluated the efficacy of individualized prophylactic treatment; determined hemostatic efficacy in the treatment of bleeding episodes; and determined hemostatic efficacy during perioperative management in subjects undergoing surgical procedures. The study enrolled a total of 71 previously treated male pediatric patients with severe hemophilia A (<1% endogenous FVIII activity or a genetic mutation consistent with severe hemophilia A). Of the 71 enrolled subjects, 69 received at least 1 dose of ELOCTATE and were evaluable for efficacy. All subjects were less than 12 years of age (35 were 1 to 5 years of age and 34 were 6 to 11 years of age).

The extension study evaluated the safety and efficacy of prophylactic treatment regimens or on-demand treatment; as well as hemostatic efficacy during perioperative management in subjects undergoing surgical procedures. The study enrolled a total of 240 previously treated male patients (aged 2 to 66 years old) with severe hemophilia A who completed the adult and adolescent study or the pediatric study.

On-demand Treatment and Control of Bleeding Episodes

In the adult and adolescent study, a total of 757 bleeding episodes in 106 subjects were treated with ELOCTATE. The majority of the bleeding episodes were spontaneous and localized in joints. The median dose per injection used to treat a bleeding episode was 27.35 (IQR 22.73, 32.71) IU/kg. Assessment of response to each injection was recorded by subjects at 8-12 hours after treatment. A 4-point rating scale of excellent, good, moderate, and no response was used to assess response. Efficacy in control of bleeding episodes in subjects ≥12 years of age is summarized in Table 6.

Table 6: ELOCTATE Efficacy in Control of Bleeding in Subjects ≥12 Years of Age
New bleeding episodes |  | (n=757)
# of Injections to treat bleeding episodes
 | 1 injection | 661 (87.3%)
 | 2 injections | 79 (10.4%)
 | >2 injections | 17 (2.2%)
Response to first injection [Excellent: abrupt pain relief and/or improvement in bleeding; Good: definite pain relief and/or improvement in signs of bleeding but possibly requiring more than one injection; Moderate: probable beneficial effect and requiring more than one injection; No response: no improvement or condition worsens. Response evaluated at approximately 8-12 hours after treatment.] |  | (n=745)
 | Excellent or good | 78.1%
 | Moderate | 21.2%
 | No response | 0.7%

In the pediatric study, a total of 86 bleeding episodes in 69 pediatric subjects were treated with ELOCTATE. Assessment of response to each injection was recorded by subjects at 8 to 12 hours post-treatment. A 4-point rating scale of excellent, good, moderate, and no response was used to assess response. Efficacy in control of bleeding episodes in subjects <12 years of age is summarized in Table 7.

The hemostatic efficacy in treatment of bleeds was rated excellent or good in 92.6% for all evaluable first injections.

Table 7: ELOCTATE Efficacy in Control of Bleeding in Pediatric Subjects <12 Years of Age
 |  | 1-5 Years (n=35) | 6 to 11 Years (n=34) | Total (<12 Years) (n=69)
New bleeding episodes |  | (n=38) | (n=48) | (n=86)
# of Injections to treat bleeding episodes | 1 injection | 29 (76.3%) | 41 (85.4%) | 70 (81.4%)
# of Injections to treat bleeding episodes | 2 injections | 7 (18.4%) | 3 (6.3%) | 10 (11.6%)
# of Injections to treat bleeding episodes | >2 injections | 2 (5.3%) | 4 (8.3%) | 6 (7.0%)
Median dose per injection (IU/kg) to treat a bleeding episode (IQR) |  | 51.35 (29.94, 59.52) | 48.15 (29.08, 55.97) | 49.69 (29.41, 56.82)
Median total dose (IU/kg) to treat a bleeding episode (IQR) |  | 56.40 (29.94, 72.46) | 53.49 (29.08, 66.80) | 54.90 (29.41, 71.09)
Response to first injection [Excellent: abrupt pain relief and/or improvement in bleeding; Good: definite pain relief and/or improvement in signs of bleeding but possibly requiring more than one injection; Moderate: probable beneficial effect and requiring more than one injection; No response: no improvement or condition worsens. Response evaluated at approximately 8-12 hours after treatment.] |  | (n=35) | (n=46) | (n=81)
Response to first injection [Excellent: abrupt pain relief and/or improvement in bleeding; Good: definite pain relief and/or improvement in signs of bleeding but possibly requiring more than one injection; Moderate: probable beneficial effect and requiring more than one injection; No response: no improvement or condition worsens. Response evaluated at approximately 8-12 hours after treatment.] | Excellent or good | 32 (91.4%) | 43 (93.5%) | 75 (92.6%)
Response to first injection [Excellent: abrupt pain relief and/or improvement in bleeding; Good: definite pain relief and/or improvement in signs of bleeding but possibly requiring more than one injection; Moderate: probable beneficial effect and requiring more than one injection; No response: no improvement or condition worsens. Response evaluated at approximately 8-12 hours after treatment.] | Moderate | 3 (8.6%) | 1 (2.2%) | 4 (4.9%)
Response to first injection [Excellent: abrupt pain relief and/or improvement in bleeding; Good: definite pain relief and/or improvement in signs of bleeding but possibly requiring more than one injection; Moderate: probable beneficial effect and requiring more than one injection; No response: no improvement or condition worsens. Response evaluated at approximately 8-12 hours after treatment.] | No response | 0 (0.0%) | 2 (4.3%) | 2 (2.5%)

Perioperative Management

Major surgeries

Hemostasis was assessed in forty-five (45) surgeries in thirty-two (32) subjects from the adult and adolescent study and the extension study. There were no major surgeries in the pediatric study or the pharmacokinetics studies. Of the 45 major surgeries, 36 surgeries (80.0%) required a single perioperative dose to maintain hemostasis. Of the 42 major surgeries treated with at least one dose, the median average dose per injection to maintain hemostasis during surgery was 59.1 IU/kg (range 35-111). On the day of surgery, most subjects received a second injection. The total dose on the day of surgery ranged from 37.6-157.9 IU/kg.

Hemostatic response was assessed by the investigator using ordinal scales as follows:

Excellent: Intraoperative and postoperative blood loss similar to (or less than) the nonhemophilic patient. No extra doses of rFVIIIFc needed and blood component transfusions required are similar to nonhemophilic patient

Good: Intraoperative and/or postoperative bleeding slightly increased over expectations for the nonhemophilic patient, but the difference was not clinically significant. Intraoperative blood loss no more than 250 mL greater than expected for a nonhemophilic patient and no extra doses of rFVIIIFc needed and blood component transfusions required are similar to nonhemophilic patient

Fair: Intraoperative and/or postoperative blood loss is increased over expectation for the nonhemophilic patient and additional treatment was needed. Intraoperative blood loss 250 to 500 mL greater than expected for person without hemophilia or extra dose of rFVIIIFc needed or increased blood component transfusion requirement

Poor/none: Significant intraoperative and/or postoperative bleeding that was substantially increased over expectations for the nonhemophilic patient, required intervention, and was not explained by a surgical/medical issue other than hemophilia: Intraoperative blood loss >500 mL greater than for the nonhemophilic patient or unexpected hypotension or unexpected transfer to intensive care unit due to bleeding or substantially increased blood component transfusion requirement.

For forty-one (41) major surgeries in twenty-nine (29) subjects, hemostatic response was assessed and rated as excellent in 38 (93%) surgeries and good in 3 (7%) surgeries.

Types of surgeries assessed include major orthopedic procedures such as joint replacements (bilateral knee, as well as unilateral elbow, hip and knee replacements), ankle fusion and amputation. Other major surgeries include appendectomy, arthroscopy, spinal surgery, and inguinal hernia repair.

Minor surgeries

A hemostatic assessment of 72 minor surgical procedures in 59 subjects from all three studies was conducted with all (100%) having excellent or good response (excellent response [61 of 72; 84.7%] and good response [11 of 72; 15.3%]).

Routine Prophylaxis

Adult and adolescent study

The efficacy of routine prophylaxis was evaluated against on-demand treatment. A total of 117 subjects received an individualized, twice weekly regimen, which started with 25 IU/kg on the first day followed by 50 IU/kg on the fourth day. The dose and interval were adjusted within the range of 25-65 IU/kg every 3-5 days to maintain trough levels between 1% and 3% above baseline, or higher, as clinically indicated to prevent bleeding. The median dosing interval was 3.5 days. Among the 112 subjects treated for at least 6 months, 111 (99%) achieved a dosing interval of three days or longer, 39 (35%) achieved a dosing interval of 4 days or longer, and 33 (29%) achieved a dosing interval of 5 days or longer during the last 3 months on study. Twenty-three subjects received 65 IU/kg of ELOCTATE once weekly for a median period of 28 weeks. An additional 23 subjects received episodic (on-demand) doses of ELOCTATE for the treatment of bleeding episodes and were on study for a median period of 29 weeks. Using a negative binomial model to analyze the annualized bleeding rate (ABR), there was a statistically significant reduction in ABR of 92% (p<0.001) for subjects in the individualized prophylaxis arm and a statistically significant reduction of 76% (p<0.001) for subjects in the weekly prophylaxis arm compared to the episodic (on-demand) arm. Fifty-three (53) of 117 (45%) subjects experienced no bleeding episodes while on individualized prophylaxis and 4 of 23 (17%) subjects experienced no bleeding episodes while on weekly prophylaxis.

Median ABRs in subjects evaluable for efficacy is summarized in Table 8.

Table 8: Median (IQR) [Median (interquartile range, 25th and 75th percentiles)] Annualized Bleed Rate by ELOCTATE Treatment Arm in Subjects ≥12 Years of Age
Bleeding Episode Etiology | Individualized Prophylaxis (N=117) | Episodic (On-Demand) (N=23)
Overall ABR | 1.6 | 33.6
Overall ABR | (0.0, 4.7) | (21.1, 48.7)
Spontaneous ABR | 0.0 | 20.2
Spontaneous ABR | (0.0, 2.0) | (12.2, 36.8)
Joint ABR | 0.0 | 22.8
Joint ABR | (0.0, 3.1) | (15.1, 39.0)

Pediatric study

Sixty-nine (69) subjects received ELOCTATE on an individualized prophylactic dose regimen starting with a twice weekly regimen consisting of 25 IU/kg on the first day followed by 50 IU/kg on the fourth day. The dose could be adjusted within the range of 25-80 IU/kg with a minimum dosing interval of every 2 days to maintain trough of 1% above baseline or as clinically indicated to prevent bleeding. The median dosing interval was 3.49 days (interquartile range, 3.46 to 3.51 days) with no difference in the median dosing interval between age cohorts. 89.9% of subjects remained on a twice weekly interval. The median weekly dose of ELOCTATE for subjects 1-5 years of age was 91.63 IU/kg (interquartile range (IQR), 84.72 to 104.56 IU/kg). For subjects in the 6 to 11 years of age cohort, the median weekly dose was 86.88 IU/kg (IQR, 79.12 to 103.08 IU/kg).

Of all subjects, 32 (46.4%) experienced no bleeding episodes (18 subjects (51.4%) 1-5 years of age and 14 subjects (41.2%) 6 to 11 years of age). A presentation of the median ABRs evaluable for efficacy is summarized in Table 9.

Table 9: Median (IQR) [Median (interquartile range, 25th and 75th percentiles)] Annualized Bleed Rate in Pediatric Subjects <12 Years of Age
Bleeding Episode Etiology | 1-5 Years (N=35) | 6 to 11 Years (N=34) | Total (<12 Years) (N=69)
Overall ABR | 0.0 | 2.0 | 2.0
Overall ABR | (0.0, 4.0) | (0.0, 4.0) | (0.0, 4.0)
Spontaneous ABR | 0.0 | 0.0 | 0.0
Spontaneous ABR | (0.0, 0.0) | (0.0, 0.0) | (0.0, 0.0)
Joint ABR | 0.0 | 0.0 | 0.0
Joint ABR | (0.0, 1.9) | (0.0, 2.0) | (0.0, 2.0)

15 REFERENCES

1. Sommer JM, Moore N, McGuffie-Valentine B, et al. Comparative field study evaluating the activity of recombinant factor VIII Fc fusion protein in plasma samples at clinical haemostasis laboratories. Haemophilia. 2014;20:294–300.

16 HOW SUPPLIED/STORAGE AND HANDLING

How Supplied

ELOCTATE is supplied in kits comprising a single-dose vial containing nominally, 250, 500, 750, 1000, 1500, 2000, 3000, 4000, 5000 or 6000 international units (IU) of Factor VIII potency, a pre-filled syringe with 3 mL sterile water for injection, and a sterile vial adapter (reconstitution device). The actual amount of ELOCTATE in IU is stated on the label and carton of each vial.

Not made with natural rubber latex.

Strength | Potency Color Code | Kit NDC Number
250 IU | Yellow | 71104-801-01
500 IU | Red | 71104-802-01
750 IU | Garnet | 71104-803-01
1000 IU | Green | 71104-804-01
1500 IU | Dark Green | 71104-805-01
2000 IU | Royal Blue | 71104-806-01
3000 IU | Mist Grey | 71104-807-01
4000 IU | Orange | 71104-808-01
5000 IU | Mist Brown | 71104-809-01
6000 IU | Purple | 71104-810-01

Storage and Handling

Prior to reconstitution:

- Store ELOCTATE in the original package to protect the ELOCTATE vials from light.
- Store ELOCTATE in powder form at 2°C to 8°C (36°F to 46°F). Do not freeze to avoid damage to the pre-filled diluent syringe.
- ELOCTATE may be stored at room temperature, not to exceed 30°C (86°F), for a single period of up to 6 months, within the expiration date printed on the label.
- If stored at room temperature, record the date that ELOCTATE is removed from refrigeration on the carton in the area provided. After storage at room temperature, do not return the product to the refrigerator.
- Do not use beyond the expiration date printed on the vial or 6 months after the date that was written on the carton, whichever is earlier.

After Reconstitution:

- The reconstituted product may be stored at room temperature, not to exceed 30°C (86°F), for up to 3 hours. Protect from direct sunlight. After reconstitution, if the product is not used within 3 hours, it must be discarded.
- Do not use ELOCTATE if the reconstituted solution is cloudy or has particulate matter.
- Discard any unused ELOCTATE.

17 PATIENT COUNSELING INFORMATION

Advise the patients to:

- Read the FDA approved patient labeling (Patient Information and Instructions for Use).
- Call their healthcare provider or go to the emergency department right away if a hypersensitivity reaction occurs. Early signs of hypersensitivity reactions may include rash, hives, itching, facial swelling, tightness of the chest, and wheezing.
- Contact their healthcare provider or treatment facility for further treatment and/or assessment if they experience a lack of a clinical response to Factor VIII therapy because this may be a sign of inhibitor development.

Manufactured by:
Bioverativ Therapeutics Inc.
Waltham, MA 02451
A SANOFI COMPANY
US License Number 2078
©2023 Bioverativ Therapeutics Inc. All rights reserved.

ELOCTATE® is a registered trademark of Bioverativ Therapeutics Inc.

For patent information: https://www.sanofi.us/en/products-and-resources/patents

Patient Information

ELOCTATE® /el' ok' tate /

[Antihemophilic Factor (Recombinant), Fc Fusion Protein]

Please read this Patient Information carefully before using ELOCTATE and each time you get a refill, as there may be new information. This Patient Information does not take the place of talking with your healthcare provider about your medical condition or your treatment.

What is ELOCTATE?

ELOCTATE is an injectable medicine that is used to help control and prevent bleeding in people with Hemophilia A (congenital Factor VIII deficiency).

Your healthcare provider may give you ELOCTATE when you have surgery.

Who should not use ELOCTATE?

You should not use ELOCTATE if you had an allergic reaction to it in the past.

What should I tell my healthcare provider before using ELOCTATE?

Talk to your healthcare provider about:

- Any medical problems that you have or had.
- All prescription and non-prescription medicines that you take, including over-the-counter medicines, supplements or herbal medicines.
- Pregnancy or if you are planning to become pregnant. It is not known if ELOCTATE may harm your unborn baby.
- Breastfeeding. It is not known if ELOCTATE passes into the milk and if it can harm your baby.

How should I use ELOCTATE?

You get ELOCTATE as an infusion into your vein. Your healthcare provider will instruct you on how to do infusions on your own, and may watch you give yourself the first dose of ELOCTATE.

Contact your healthcare provider right away if bleeding is not controlled after using ELOCTATE.

What are the possible side effects of ELOCTATE?

You can have an allergic reaction to ELOCTATE. Call your healthcare provider or emergency department right away if you have any of the following symptoms: difficulty breathing, chest tightness, swelling of the face, rash or hives.

Your body can also make antibodies called "inhibitors" against ELOCTATE. This can stop ELOCTATE from working properly. Your healthcare provider may give you blood tests to check for inhibitors.

Additional common side effects of ELOCTATE are headache, rash, joint pain, muscle pain, and general discomfort.

If you have risk factors for developing abnormal blood clots in your body, such as an indwelling venous catheter, treatment with Factor VIII may increase this risk.

These are not the only possible side effects of ELOCTATE. Tell your healthcare provider about any side effect that bothers you or does not go away.

How should I store ELOCTATE?

- Keep ELOCTATE in its original package.
- Protect it from light.
- Do not freeze.
- Store refrigerated (2°C to 8°C or 36°F to 46°F) or at room temperature [not to exceed 30°C (86°F)], for up to six months.
- When storing at room temperature:
  - Note on the carton the date on which the product is removed from refrigeration.
  - Use the product before the end of this 6-month period or discard it.
  - Do not return the product to the refrigerator.

Do not use ELOCTATE after the expiration date printed on the vial or, if you removed it from the refrigerator, after the date that was noted on the carton, whichever is earlier.

After reconstitution (mixing with the diluent):

- Do not use ELOCTATE if the reconstituted solution is not clear to slightly opalescent and colorless.
- Use reconstituted product as soon as possible.
- You may store reconstituted solution at room temperature, not to exceed 30°C (86°F), for up to three hours. Protect the reconstituted product from direct sunlight. Discard any product not used within three hours.

What else should I know about ELOCTATE?

Medicines are sometimes prescribed for purposes other than those listed here. Do not use ELOCTATE for a condition for which it was not prescribed. Do not share ELOCTATE with other people, even if they have the same symptoms that you have.

This Patient Information has been approved by the US Food and Drug Administration.

Manufactured by:
Bioverativ Therapeutics Inc.
Waltham, MA 02451
A SANOFI COMPANY
US License Number 2078
©2023 Bioverativ Therapeutics Inc. All rights reserved.

ELOCTATE® is a registered trademark of Bioverativ Therapeutics Inc.
Revised: May 2023

INSTRUCTIONS FOR USE

ELOCTATE®

Antihemophilic Factor (Recombinant), Fc Fusion Protein

INSTRUCTIONS FOR USE

Read the Instructions for Use before you start using ELOCTATE and each time you get a refill. There may be new information. This information does not take the place of talking to your healthcare provider about your medical condition or your treatment.

Your healthcare provider should show you or your caregiver how to reconstitute and administer ELOCTATE the first time ELOCTATE is used.

Check the expiration date on the ELOCTATE kit.

Do not use the product if past the expiration date.

Allow the ELOCTATE vial and the diluent to come to room temperature.

Do not use external heat sources such as putting the vial and/or diluent in hot water.

Find a clean, flat work surface and collect all the supplies you will need to reconstitute and administer ELOCTATE.

Wash your hands with soap and water. Aseptic technique (clean and germ free) should be used.

YOUR KIT CONTAINS:

RECONSTITUTION

Step 1
Remove the plastic cap from the ELOCTATE vial.
Wipe the rubber stopper of the vial with an alcohol wipe and allow it to dry.
After cleaning, do not touch the rubber stopper with your hand or allow it to touch any surface.

Step 2
Completely remove the backing from the vial adapter package by peeling back the lid.
Do not remove the vial adapter from the package or touch the inside of the vial adapter.

Step 3
Keep the vial on a flat surface. Hold the vial adapter package with one hand and using the other hand, place the vial adapter over the vial.
The spike should be placed directly above the center of the rubber stopper.
Push the vial adapter straight down until the adapter spike punctures the center of the vial stopper and is fully inserted.

Step 4
Lift the package cover away from the vial adapter and discard the cover.

Step 5
Only use the diluent syringe provided to reconstitute the drug product.
Hold the plunger rod at the circular disk.
Place the tip of the plunger rod into the end of the syringe.
Turn in a clockwise motion until it is securely attached.

Step 6
With one hand, hold the diluent syringe right under the cap, and with the cap pointing up.
Make sure you are holding the diluent syringe by the ridged part directly under the cap.
Do not use if the cap has been removed or is not securely attached.

Step 7
With your other hand, grasp the cap and bend it at a 90° angle until it snaps off.
After the cap snaps off, you will see the glass tip of the syringe.
Do not touch the glass tip of the syringe or inside of the cap.

Step 8
Be sure the vial is sitting on a flat surface.
Insert the tip of the syringe into the adapter opening.
Turn the syringe in a clockwise motion until it is securely attached to the adapter.

Step 9
Slowly depress the plunger rod to inject all of the diluent into the vial.
The plunger rod may rise slightly after this process. This is normal.

Step 10
With the syringe still connected to the adapter, gently swirl the vial until the product is completely dissolved.
The appearance of the solution should be clear to slightly opalescent and colorless.
Do not shake.
Do not use the reconstituted ELOCTATE if it contains visible particles or is cloudy.

Step 11
Make sure the plunger rod is completely depressed.
Turn the vial upside-down.
Slowly pull on the plunger rod to draw the solution into the syringe.
Be careful not to pull the plunger rod completely out of the syringe.

Step 12
Gently unscrew the syringe from the vial adapter and dispose of the vial with the adapter still attached.
Do not touch the syringe tip or the inside of the cap.
Reconstituted ELOCTATE should be administered as soon as possible.

POOLING

POOLING is the process of combining two or more reconstituted vials into a larger syringe (not into the diluent syringe) prior to intravenous administration.

If you are using two or more vials, follow these pooling steps.

Be sure to leave the vial adapter attached to the vial as you will need it for attaching a large luer lock syringe.

Do not detach the diluent syringe or the large luer syringe until you are ready to attach the large luer lock syringe to the next vial (with vial adapter attached).

Step 1
Remove the diluent syringe from the vial adapter by turning it counterclockwise until it is completely detached.

Step 2
Attach a separate large luer lock syringe by turning clockwise until it is securely attached.

Step 3
Slowly pull on the plunger rod to draw the solution into the syringe.
Repeat this pooling procedure with each vial you will be using.
Once you have pooled the required dose, proceed to administration using the large luer lock syringe.

ADMINISTRATION (Intravenous Injection)

ELOCTATE is administered by intravenous infusion after reconstitution of the drug powder with the diluent.

Your healthcare provider should teach you how to infuse ELOCTATE. Once you have been taught to self-infuse, you can follow these instructions.

Do not administer reconstituted ELOCTATE if it contains particulate matter, is discolored, or is cloudy.

Step 1
Attach the syringe to the connector end of the infusion set tubing by turning clockwise until it is securely attached.
Do not administer reconstituted ELOCTATE in the same tubing or container with other medicinal products.

Step 2
Apply a tourniquet and clean the skin area where you will perform the infusion using an alcohol wipe.

Step 3
Depress the plunger until all air is removed from the syringe and ELOCTATE has reached the end of the infusion set tubing.
Do not push ELOCTATE through the needle.

Step 4
Remove the protective needle cover from the infusion set tubing.
Insert the needle on the infusion set tubing into the vein.
Remove the tourniquet.
Always verify proper needle placement when performing intravenous administration.

Step 5
Slowly depress the plunger on the syringe to administer ELOCTATE.
ELOCTATE should be injected intravenously over several minutes.
The rate of administration should be determined by your comfort level.
The small amount of drug product left in the infusion set will not affect treatment.

Step 6
After infusing ELOCTATE, remove the infusion set and use a sterile gauze to put pressure on the infusion site for several minutes.
Apply an adhesive bandage if necessary.
Dispose of all unused solution, empty vial(s), and other used medical supplies in an appropriate medical waste container.

STORAGE CONDITIONS - PRODUCT KIT

Keep refrigerated until use.
Keep away from direct sunlight.

STORAGE CONDITIONS - RECONSTITUTED

ELOCTATE should be administered within 3 hours after reconstitution.

Do not refrigerate after reconstitution.

Keep away from direct sunlight.

This Instructions for Use has been approved by the US Food and Drug Administration.

Manufactured by:
Bioverativ Therapeutics Inc.
Waltham, MA 02451
A SANOFI COMPANY
US License Number 2078
©2023 Bioverativ Therapeutics Inc. All rights reserved.

For more information go to www.ELOCTATE.com or call 1-855-693-5628

Revised May 2023

PRINCIPAL DISPLAY PANEL - Kit Carton - 250 IU

250 IU Nominal

NDC 71104-801-01

One single-dose vial
with 3 mL prefilled
diluent syringe

ELOCTATE®
Antihemophilic Factor
(Recombinant), Fc Fusion Protein

For Intravenous Administration

Rx Only

Manufactured by:
Bioverativ Therapeutics Inc.
Waltham, MA 02451
US License Number 2078

www.ELOCTATE.com

Bioverativ

PRINCIPAL DISPLAY PANEL - Kit Carton - 500 IU

500 IU Nominal

NDC 71104-802-01

One single-dose vial
with 3 mL prefilled
diluent syringe

ELOCTATE®
Antihemophilic Factor
(Recombinant), Fc Fusion Protein

For Intravenous Administration

Rx Only

Manufactured by:
Bioverativ Therapeutics Inc.
Waltham, MA 02451
US License Number 2078

www.ELOCTATE.com

Bioverativ

PRINCIPAL DISPLAY PANEL - Kit Carton - 750 IU

750 IU Nominal

NDC 71104-803-01

One single-dose vial
with 3 mL prefilled
diluent syringe

ELOCTATE®
Antihemophilic Factor
(Recombinant), Fc Fusion Protein

For Intravenous Administration

Rx Only

Manufactured by:
Bioverativ Therapeutics Inc.
Waltham, MA 02451
US License Number 2078

www.ELOCTATE.com

Bioverativ

PRINCIPAL DISPLAY PANEL - Kit Carton - 1000 IU

1000 IU Nominal

NDC 71104-804-01

One single-dose vial
with 3 mL prefilled
diluent syringe

ELOCTATE®
Antihemophilic Factor
(Recombinant), Fc Fusion Protein

For Intravenous Administration

Rx Only

Manufactured by:
Bioverativ Therapeutics Inc.
Waltham, MA 02451
US License Number 2078

www.ELOCTATE.com

Bioverativ

PRINCIPAL DISPLAY PANEL - Kit Carton - 1500 IU

1500 IU Nominal

NDC 71104-805-01

One single-dose vial
with 3 mL prefilled
diluent syringe

ELOCTATE®
Antihemophilic Factor
(Recombinant), Fc Fusion Protein

For Intravenous Administration

Rx Only

Manufactured by:
Bioverativ Therapeutics Inc.
Waltham, MA 02451
US License Number 2078

www.ELOCTATE.com

Bioverativ

PRINCIPAL DISPLAY PANEL - Kit Carton - 2000 IU

2000 IU Nominal

NDC 71104-806-01

One single-dose vial
with 3 mL prefilled
diluent syringe

ELOCTATE®
Antihemophilic Factor
(Recombinant), Fc Fusion Protein

For Intravenous Administration

Rx Only

Manufactured by:
Bioverativ Therapeutics Inc.
Waltham, MA 02451
US License Number 2078

www.ELOCTATE.com

Bioverativ

PRINCIPAL DISPLAY PANEL - Kit Carton - 3000 IU

3000 IU Nominal

NDC 71104-807-01

One single-dose vial
with 3 mL prefilled
diluent syringe

ELOCTATE®
Antihemophilic Factor
(Recombinant), Fc Fusion Protein

For Intravenous Administration

Rx Only

Manufactured by:
Bioverativ Therapeutics Inc.
Waltham, MA 02451
US License Number 2078

www.ELOCTATE.com

Bioverativ

PRINCIPAL DISPLAY PANEL - Kit Carton - 4000 IU

4000 IU Nominal

NDC 71104-808-01

One single-dose vial
with 3 mL prefilled
diluent syringe

ELOCTATE®
Antihemophilic Factor
(Recombinant), Fc Fusion Protein

For Intravenous Administration

Rx Only

Manufactured by:
Bioverativ Therapeutics Inc.
Waltham, MA 02451
US License Number 2078

www.ELOCTATE.com

Bioverativ

PRINCIPAL DISPLAY PANEL - Kit Carton - 5000 IU

5000 IU Nominal

NDC 71104-809-01

One single-dose vial
with 3 mL prefilled
diluent syringe

ELOCTATE®
Antihemophilic Factor
(Recombinant), Fc Fusion Protein

For Intravenous Administration

Rx Only

Manufactured by:
Bioverativ Therapeutics Inc.
Waltham, MA 02451
US License Number 2078

www.ELOCTATE.com

Bioverativ

PRINCIPAL DISPLAY PANEL - Kit Carton - 6000 IU

6000 IU Nominal

NDC 71104-810-01

One single-dose vial
with 3 mL prefilled
diluent syringe

ELOCTATE®
Antihemophilic Factor
(Recombinant), Fc Fusion Protein

For Intravenous Administration

Rx Only

Manufactured by:
Bioverativ Therapeutics Inc.
Waltham, MA 02451
US License Number 2078

www.ELOCTATE.com

Bioverativ